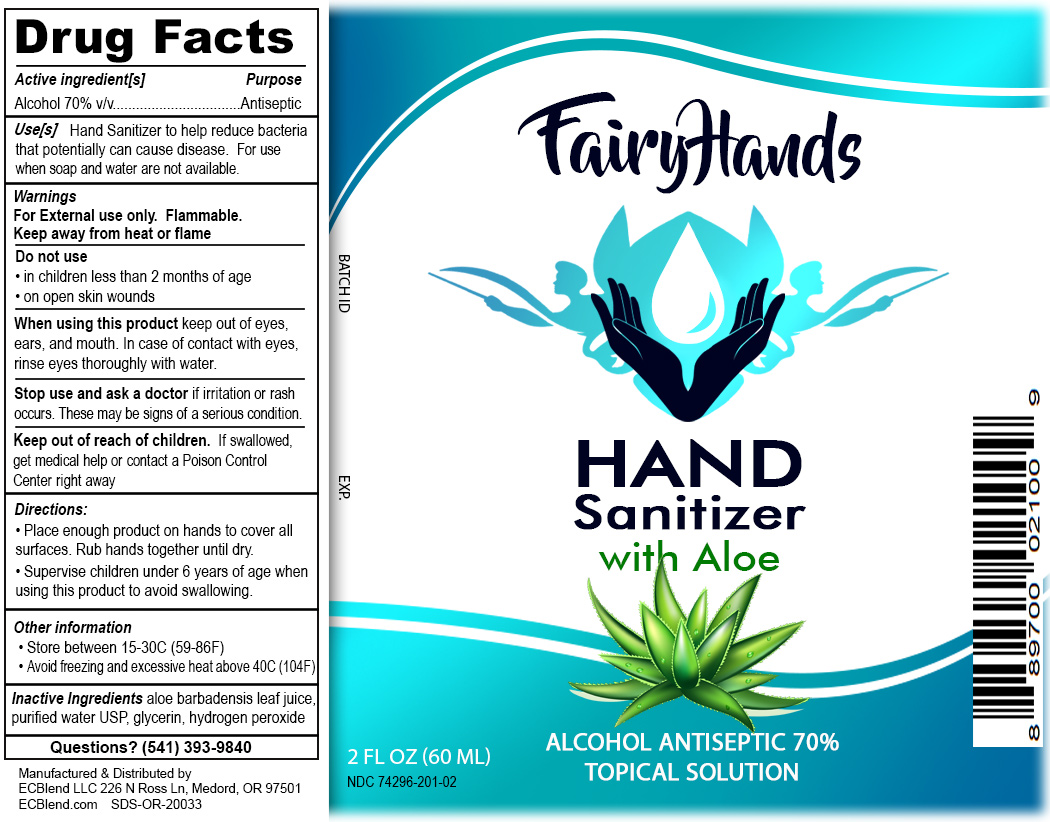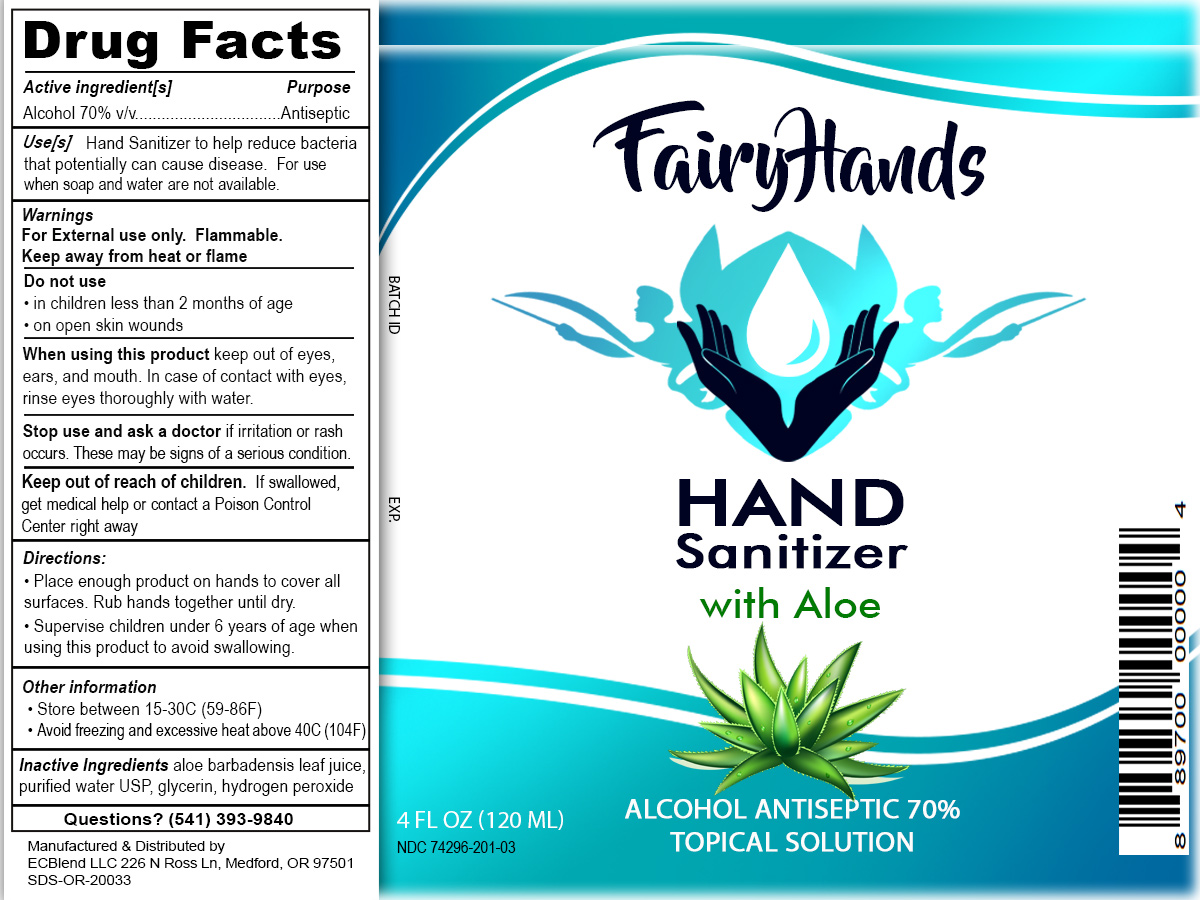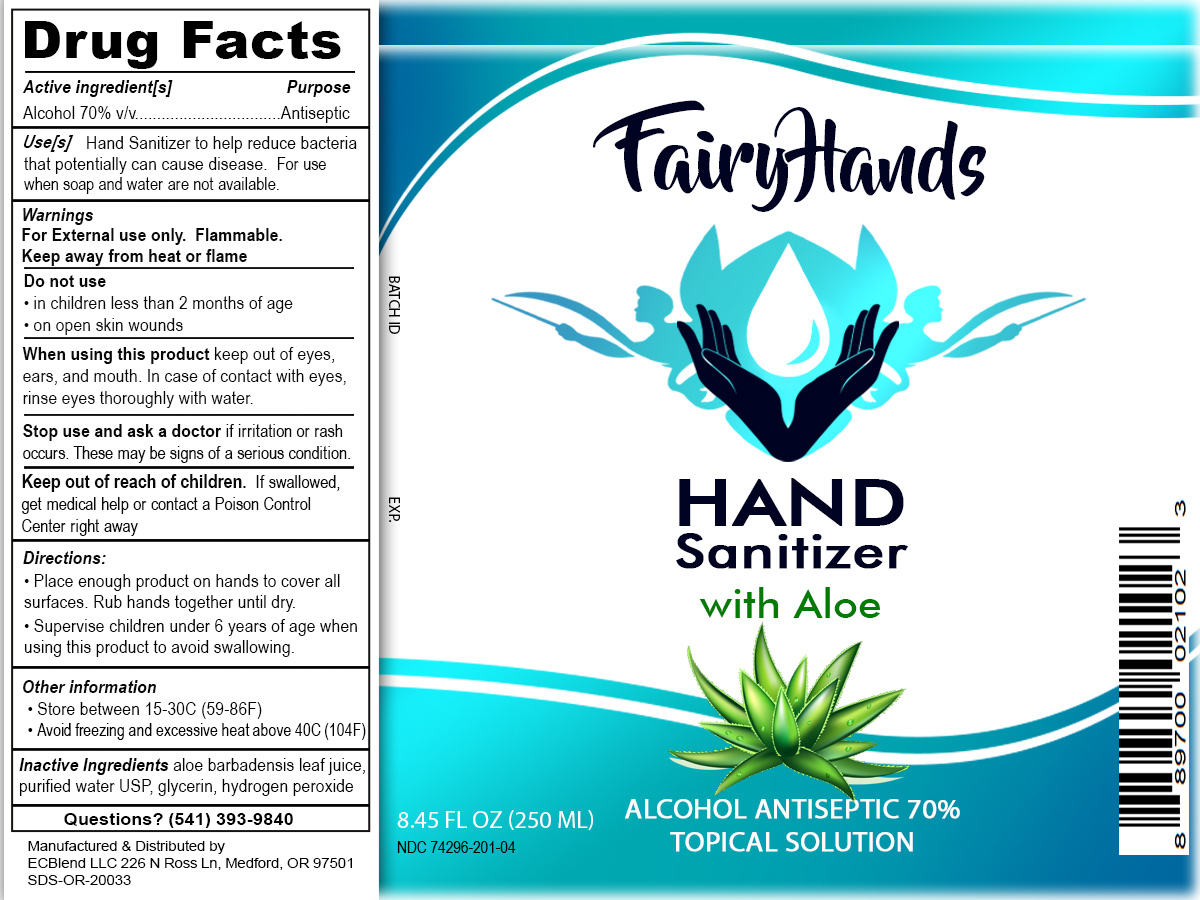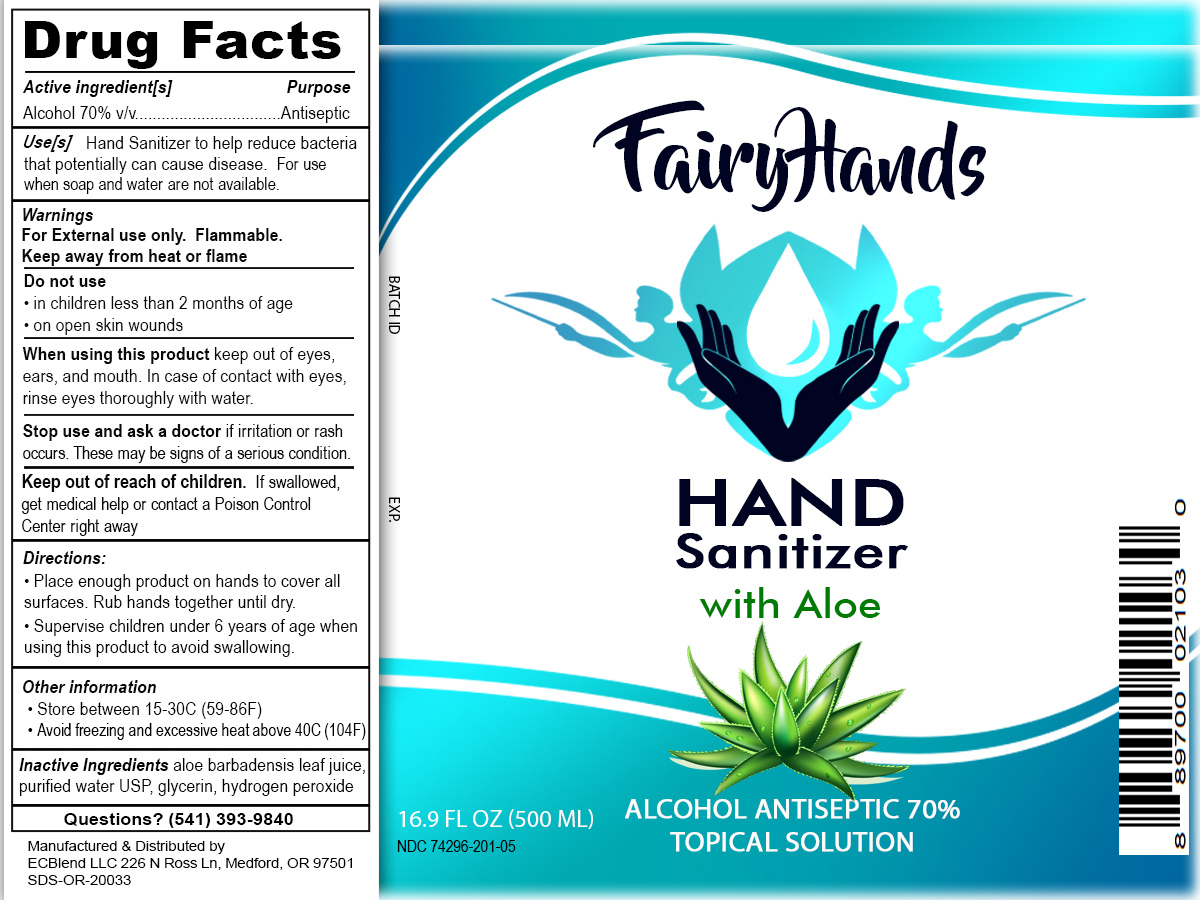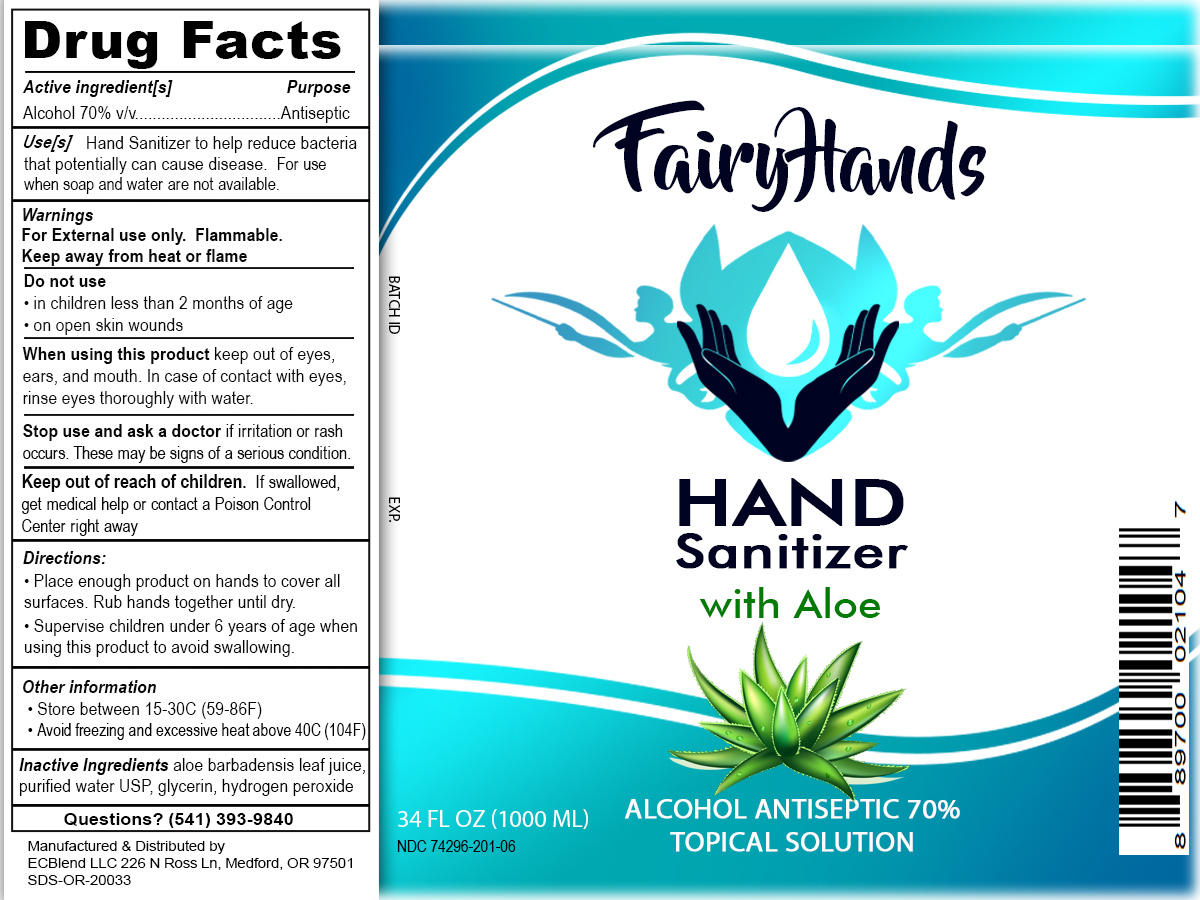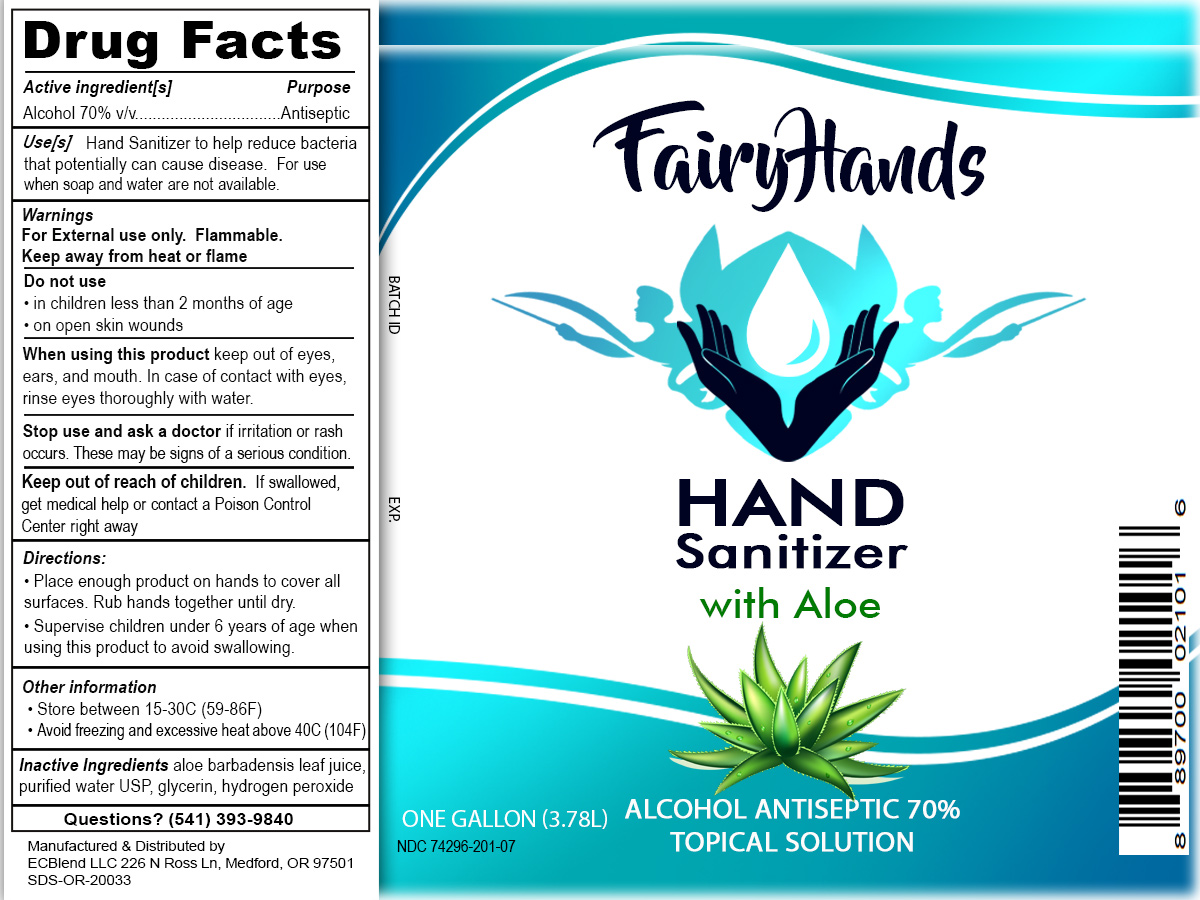 DRUG LABEL: Fairy Hands Hand Sanitizer
NDC: 74296-201 | Form: LIQUID
Manufacturer: ECBlend, LLC
Category: otc | Type: HUMAN OTC DRUG LABEL
Date: 20200501

ACTIVE INGREDIENTS: ALCOHOL 70 mL/100 mL
INACTIVE INGREDIENTS: HYDROGEN PEROXIDE 0.125 mL/100 mL; ALOE VERA LEAF 25 mL/100 mL; GLYCERIN 1.45 mL/100 mL; WATER

Hand Sanitizer

The hand sanitizer is manufactured using only the following United States Pharmacopoeia (USP) grade ingredients in the preparation of the product (percentage in final product formulation)s:

Alcohol (ethanol) (USP or Food Chemical Codex (FCC) grade) (70%, volume/volume (v/v)) in an aqueous solution denatured according to Alcohol and Tobacco Tax and Trade Bureau regulations in 27 CFR part 20.
Glycerol (1.45% v/v).
Hydrogen peroxide (0.125% v/v).
Aloe vera leaf (25% v/v).
Sterile distilled water.

Active Ingredient(s)

Alcohol 70% v/v. Purpose: Antiseptic

Purpose

Antiseptic, Hand Sanitizer

Use

Hand Sanitizer to help reduce bacteria that potentially can cause disease. For use when soap and water are not available.

Warnings

For external use only. Flammable. Keep away from heat or flame

Do not use

- in children less than 2 months of age
- on open skin wounds

When using this product keep out of eyes, ears, and mouth. In case of contact with eyes, rinse eyes thoroughly with water.
Stop use and ask a doctor if irritation or rash occurs. These may be signs of a serious condition.
Keep out of reach of children. If swallowed, get medical help or contact a Poison Control Center right away.

Stop use and ask a doctor if irritation or rash occurs. These may be signs of a serious condition.

Keep out of reach of children. If swallowed, get medical help or contact a Poison Control Center right away.

Directions

- Place enough product on hands to cover all surfaces. Rub hands together until dry.
- Supervise children under 6 years of age when using this product to avoid swallowing.

Other information

- Store between 15-30C (59-86F)
- Avoid freezing and excessive heat above 40C (104F)

Inactive ingredients

loe barbadensis leaf juice,purified water USP, glycerin, hydrogen peroxide

Package Label - Principal Display Panel

00 mL NDC: 00000-000-00

120mL NDC: 74296-201-03
60mL NDC: 74296-201-02
3785mL NDC: 74296-201-07
250mL NDC: 74296-201-04
500mL NDC: 74296-201-05
1000mL NDC: 74296-201-06